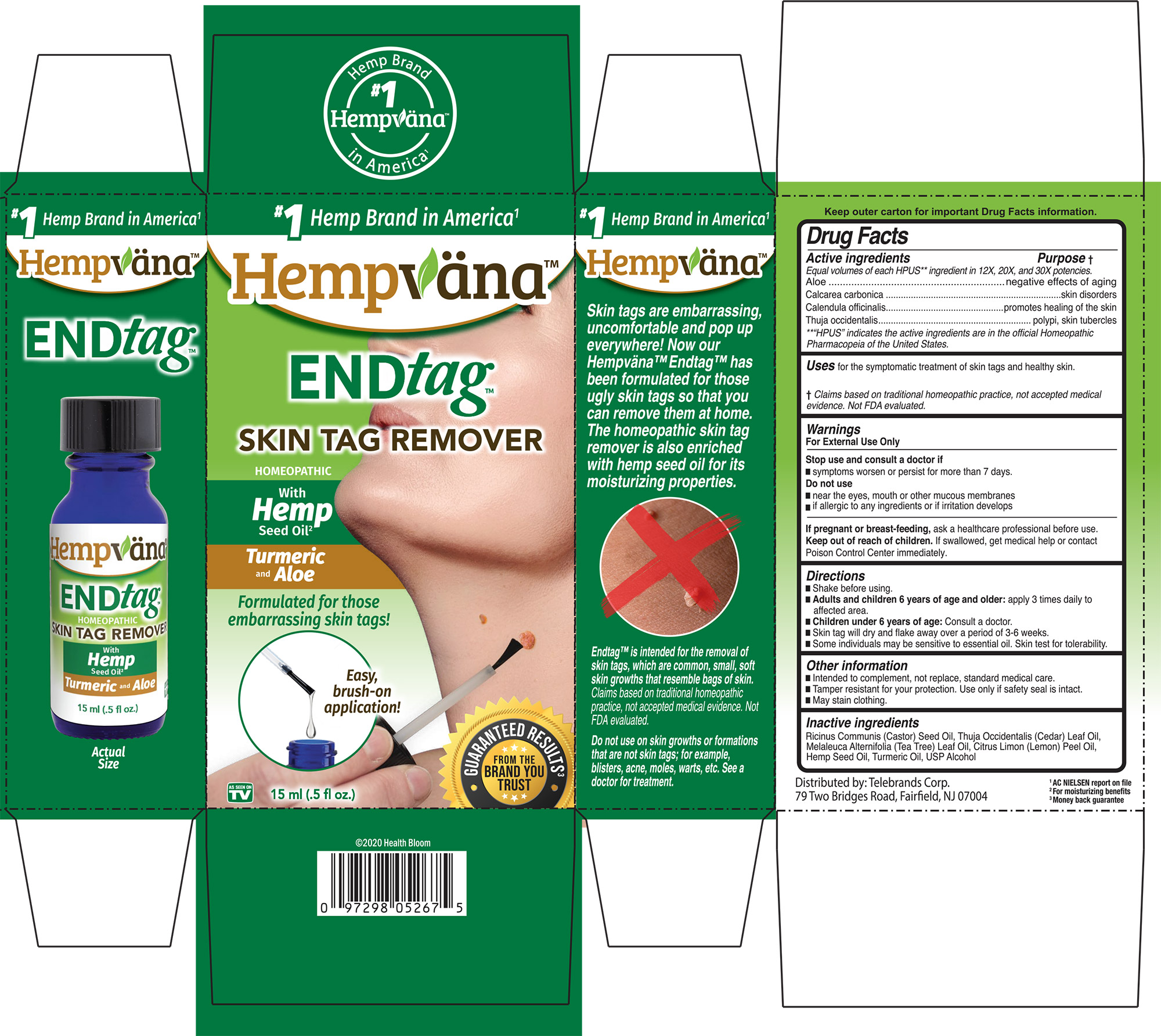 DRUG LABEL: ENDtag
NDC: 57955-9650 | Form: LIQUID
Manufacturer: King Bio Inc
Category: homeopathic | Type: HUMAN OTC DRUG LABEL
Date: 20201207

ACTIVE INGREDIENTS: CALENDULA OFFICINALIS FLOWERING TOP 12 [hp_X]/15 mL; OYSTER SHELL CALCIUM CARBONATE, CRUDE 12 [hp_X]/15 mL; ALOE SUCCOTRINA WHOLE 12 [hp_X]/15 mL; THUJA OCCIDENTALIS WHOLE 12 [hp_X]/15 mL
INACTIVE INGREDIENTS: CEDAR LEAF OIL; ALCOHOL; TURMERIC OIL; TEA TREE OIL; LEMON OIL; CANNABIS SATIVA SEED OIL; CASTOR OIL

Hempvana ENDtag

HPUS Active Ingredients

Equal Volumes of each HPUS ** ingredient in 12x, 20x, and 30x potencies.

Aloe

Calcarea carbonica

Calendula officinalis

Thuja occidentalis

**HPUS indicates the active ingredie ts are in the official Homeopathic Pharmacopeia of the United States

Active ingredients ................. Purpose

Equal volumes of each HPUS** ingredient in 12X, 20X, and 30X potencies.

Aloe...........................................negative effects of againg

Calcarea carbonica...............skin disorders

Calendula officinalis.............promotes healing of the skin

Thuja occidentalis.................polypi, skin, tubercles

**“HPUS” indicates the active ingredients are in the official Homeopathic Pharmacopeia of the United States.

Uses

for the symptomatic treatment of skin tags and healthy skin.

Claims based on traditional homeopathic practice, not accepted medical evidence. Not FDA evaluated.

Warnings

For External Use Only

Stop use and consult a doctor if

- symptoms worsen or persist for more than 7 days.

Do not use

- near the eyes, mouth or other mucous membranes
- if allergic to any ingredients or if irritation develops

PREGNANCY OR BREAST FEEDING

If pregnant or breast-feeding, ask a healthcare professional before use.

Keep out of reach of children. If swallowed, get medical help or contact Poison Control Center immediately.

Directions

- Shake before using
- Adults and children 6 years of age and older: apply 3 times daily to affected area.
- Children under 6 years of age: Consult a doctor.
- Skin tag will dry and flake away over a period of 3-6 weeks.
- Some individuals may be senstitive to essential oil. Skin test for tolerability.

Other information

- Intended to compliment, not replace, standard medcial care
- Tamper resistant for your protection. Use only if safety seal is intact.
- May stain clothing.

Inactive ingredients

Ricinus Communis (Castor) Seed Oil, Thuja Occidentalis (Cedar) Leaf Oil, Melaleuca Alternifolia (Tea Tree) Leaf Oil, Citrus Limon (Lemon) Peel Oil, Hemp Seed Oil, Turmeric Oil, USP Alcohol.

Distributed by Telebrands Corp.

79 Two Bridges Road, Fairfield, NJ 07004